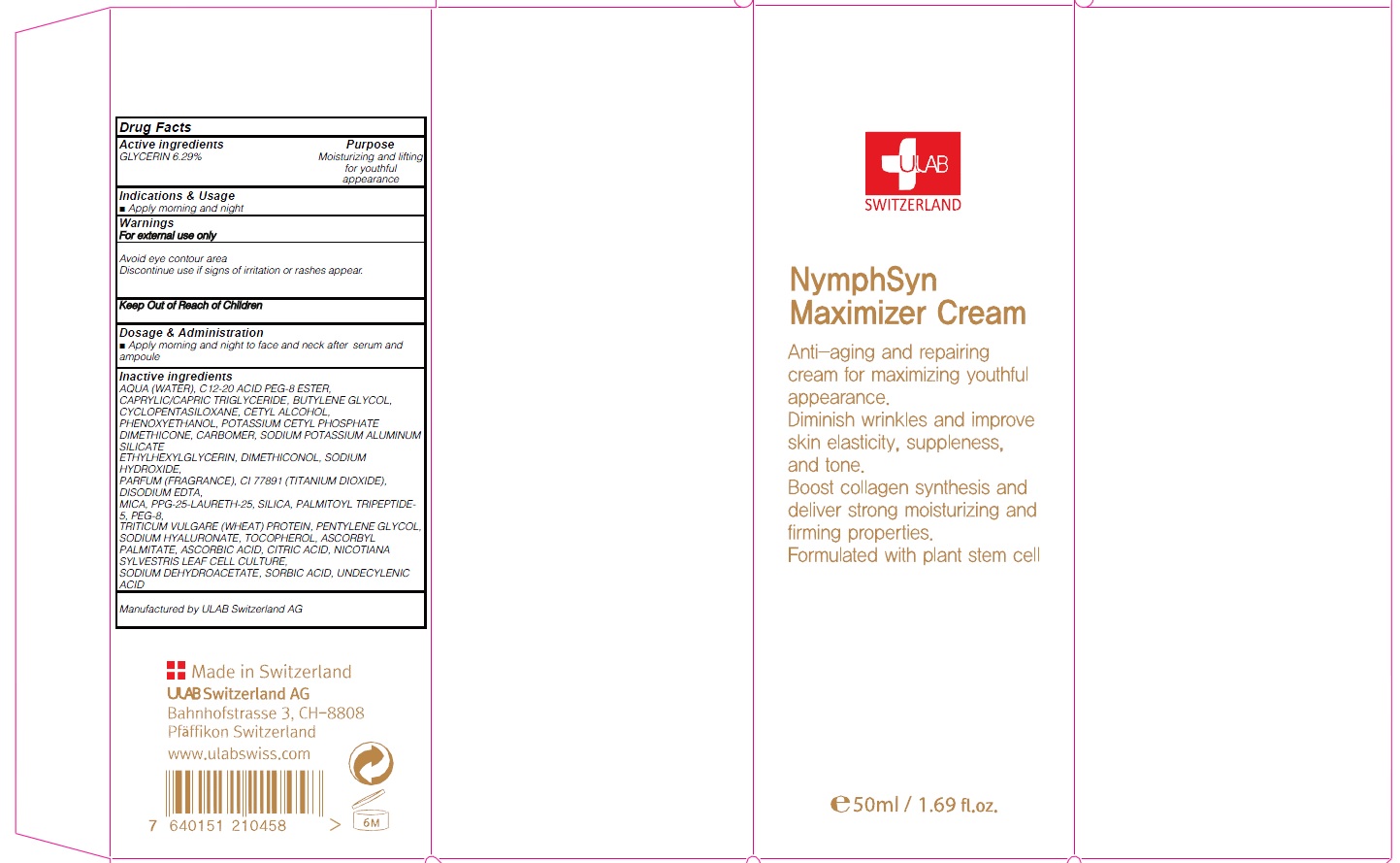 DRUG LABEL: NYMPHSYN MAXIMIZER
NDC: 71276-060 | Form: CREAM
Manufacturer: ULAB
Category: otc | Type: HUMAN OTC DRUG LABEL
Date: 20170322

ACTIVE INGREDIENTS: GLYCERIN 3.14 g/50 mL
INACTIVE INGREDIENTS: WATER; C12-20 ACID PEG-8 ESTER

ACTIVE INGREDIENT

Active ingredients: GLYCERIN 6.29%

INACTIVE INGREDIENT

Inactive ingredients: AQUA (WATER), C12-20 ACID PEG-8 ESTER, CAPRYLIC/CAPRIC TRIGLYCERIDE, BUTYLENE GLYCOL, CYCLOPENTASILOXANE, CETYL ALCOHOL, PHENOXYETHANOL, POTASSIUM CETYL PHOSPHATE DIMETHICONE, CARBOMER, SODIUM POTASSIUM ALUMINUM SILICATE ETHYLHEXYLGLYCERIN, DIMETHICONOL, SODIUM HYDROXIDE, PARFUM (FRAGRANCE), CI 77891 (TITANIUM DIOXIDE), DISODIUM EDTA, MICA, PPG-25-LAURETH-25, SILICA, PALMITOYL TRIPEPTIDE-5, PEG-8, TRITICUM VULGARE (WHEAT) PROTEIN, PENTYLENE GLYCOL, SODIUM HYALURONATE, TOCOPHEROL, ASCORBYL PALMITATE, ASCORBIC ACID, CITRIC ACID, NICOTIANA SYLVESTRIS LEAF CELL CULTURE, SODIUM DEHYDROACETATE, SORBIC ACID, UNDECYLENIC ACID

PURPOSE

Purpose: Moisturizing and lifting for youthful appearance

WARNINGS

Warnings: For external use only Avoid eye contour area Discontinue use if signs of irritation or rashes appear.

KEEP OUT OF REACH OF CHILDREN

INDICATIONS & USAGE

Indications & Usage: Apply morning and night

DOSAGE & ADMINISTRATION

Dosage & Administration: Apply morning and night to face and neck after serum and ampoule